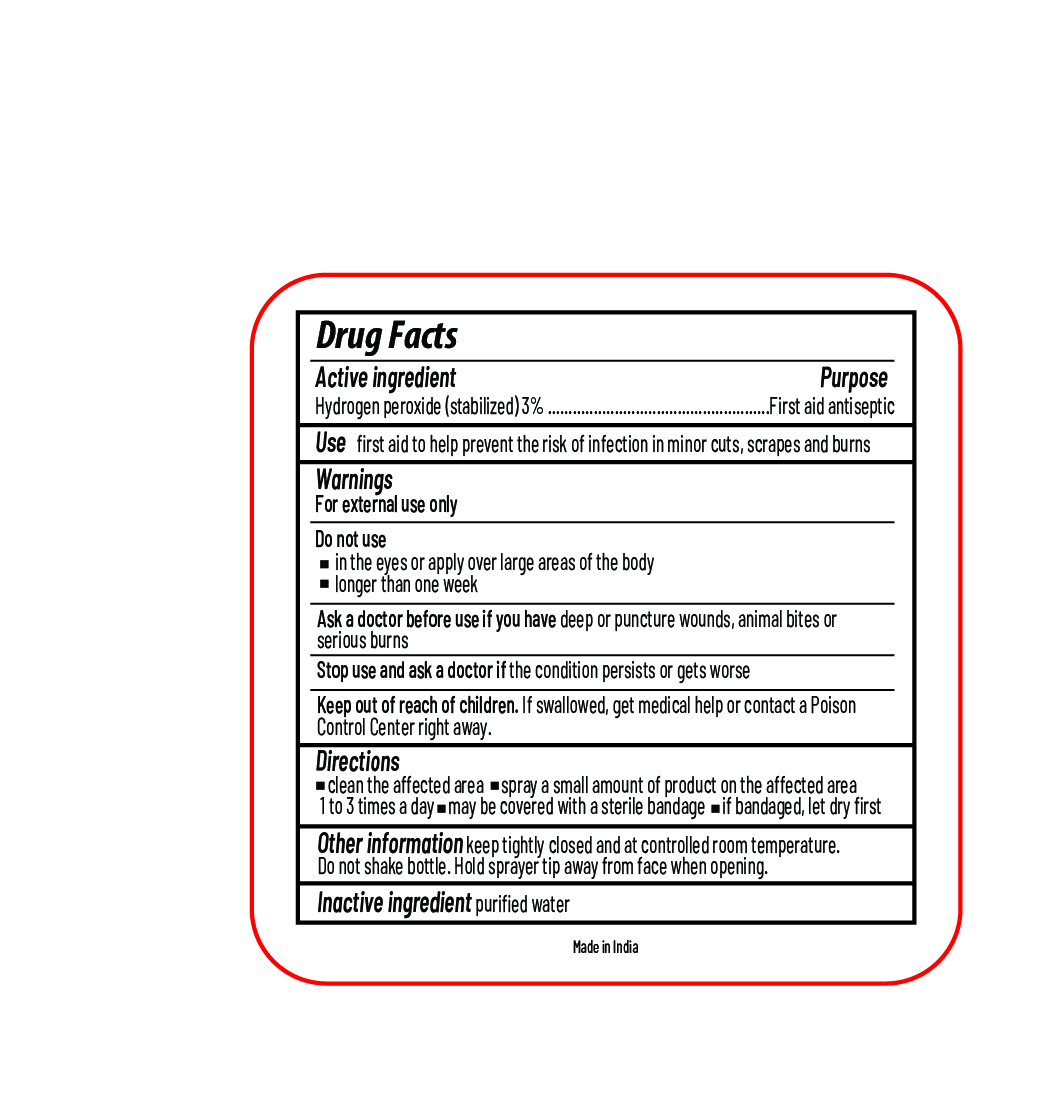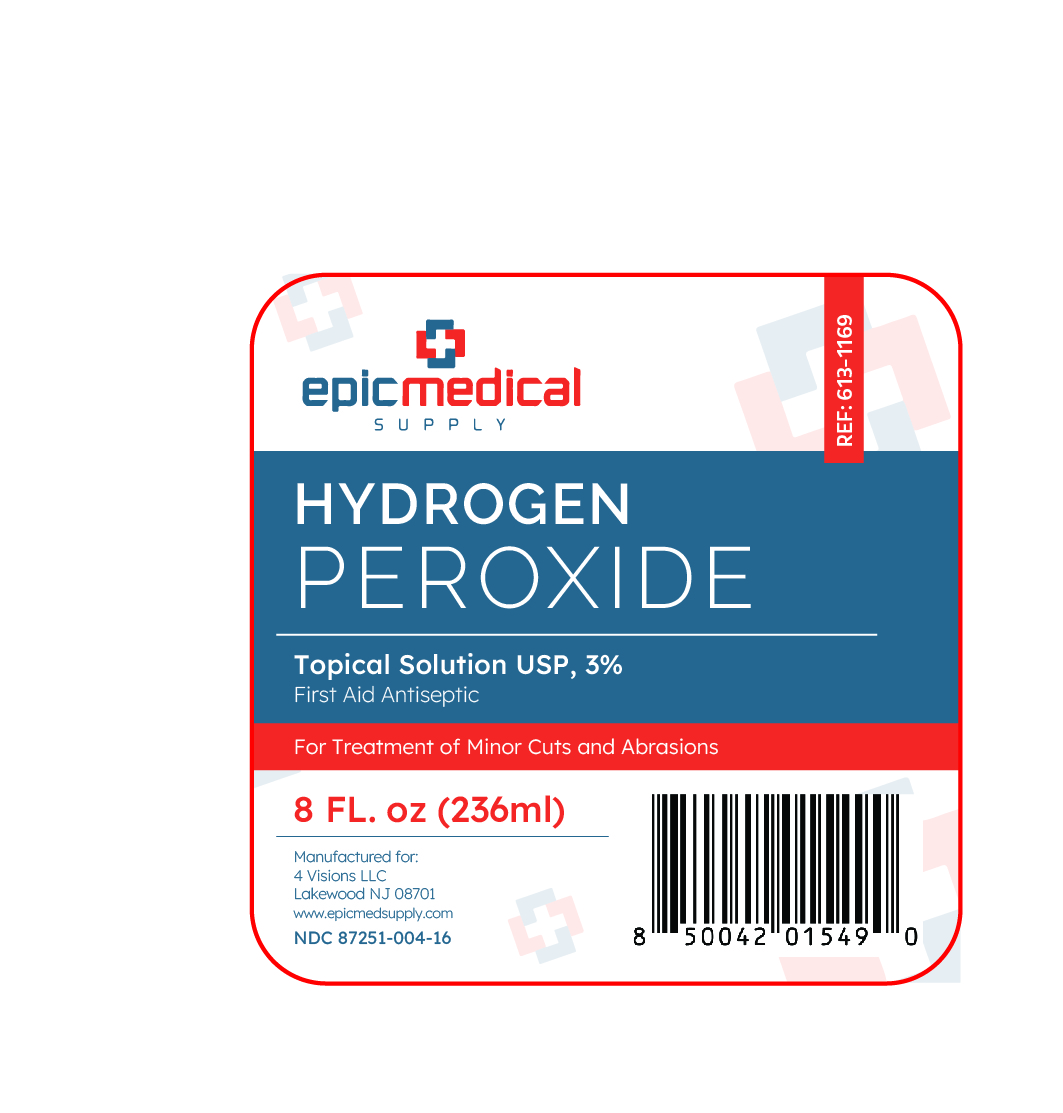 DRUG LABEL: Hydrogen Peroxide
NDC: 87251-004 | Form: LIQUID
Manufacturer: 4 Visions LLC
Category: otc | Type: HUMAN OTC DRUG LABEL
Date: 20251212

ACTIVE INGREDIENTS: HYDROGEN PEROXIDE 3 mL/100 mL
INACTIVE INGREDIENTS: WATER

Epic Medical Supply Hydrogen Peroxide Trigger Spray Bottle

Active Ingredient

Hydrogen peroxide (stabilized) 3%

Purpose

First aid antiseptic

Uses

first aid to help prevent the risk of infection in minor cuts, scrapes and burns

Warnings

For external use only

Do not use

- in eyes or apply over large areas of the body
- longer than one week

Ask a doctor before use if you have

deep or puncture wounds, animal bites or serious burns

Stop use and ask a doctor if

the condition persists or gets worse

Keep out of reach of children.

If swallowed, get medical help or contact a Poison Control Center right away.

Directions

- clean the affected area
- spray a small amount of product on the affected area 1 to 3 times a day
- may be covered with a sterile bandage
- if bandaged, let dry first

Other information

keep tightly closed and at controlled room temperature. Do not shake bottle. Hold sprayer tip away from face when opening.

Inactive ingredient

purified water

principal display panel

Epic Medical Supply

Hydrogen peroxide 3%

Manufactured for:

4 Visions LLC

Lakewood, NJ 08701

www.epicmedicalsupply.com